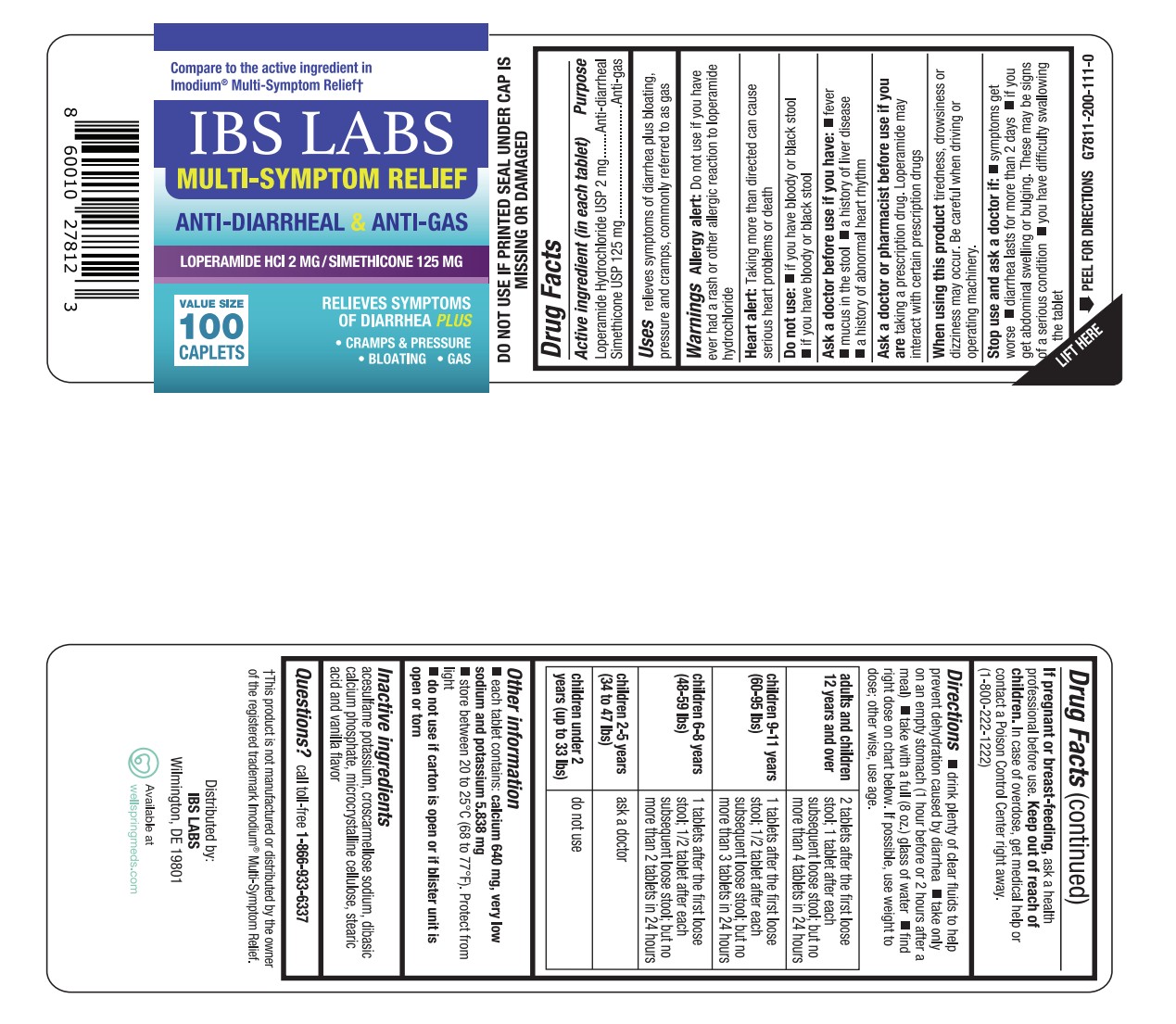 DRUG LABEL: Loperamide Hydrochloride and Simethicone
NDC: 84441-713 | Form: TABLET
Manufacturer: IMO-GEN LABS LLC
Category: otc | Type: HUMAN OTC DRUG LABEL
Date: 20251023

ACTIVE INGREDIENTS: DIMETHICONE 125 mg/1 1; LOPERAMIDE HYDROCHLORIDE 2 mg/1 1
INACTIVE INGREDIENTS: ACESULFAME POTASSIUM; CALCIUM PHOSPHATE, DIBASIC, ANHYDROUS; STEARIC ACID; CELLULOSE, MICROCRYSTALLINE; CROSCARMELLOSE SODIUM

IBS-10 Loperamide Simethicone

ACTIVE INGREDIENT(S)

(in each tablet)
Loperamide Hydrochloride USP 2 mg
Simethicone USP 125 mg

PURPOSES

Anti-diarrheal
Anti-gas

USE(S)

relieves symptoms of diarrhea plus bloating, pressure and cramps, commonly referred to as gas

WARNINGS

Allergry alert: Do not user if you have ever had a rash or other allergic reaction to loperamide hydrochloride

HEART ALERT

Taking more than directed can cause serious heart problems or death.

DO NOT USE

• if you have bloody or black stool
• if you have difficulty swallowing

ASK A DOCTOR BEFORE USE IF YOU HAVE

• fever
• mucus in the stool
• a history of liver disease

• a history of abnormal heart rhythm

ASK A DOCTOR OR PHARMACIST BEFORE USE IF

you are taking a prescription drug. Loperamide may interact with certain prescription drugs.

WHEN USING THIS PRODUCT

tiredness, drowsiness or dizziness may occur. Be careful when driving or operating machinery.

STOP USE AND ASK A DOCTOR IF

• symptoms get worse
• diarrhea lasts for more than 2 days
• you get abdominal swelling or bulging. These may be signs of a serious condition.
• you have difficulty swallowing the tablet

If pregnant or breast-feeding, ask a health professional before use.

If pregnant or breast-feeding

ask a health professional before use.

KEEP OUT OF REACH OF CHILDREN

In case of overdose, get medical help or contact a Poison Control Center right away. (1-800-222-1222)

DIRECTIONS

• drink plenty of clear fluids to help prevent dehydration caused by diarrhea
• take only on an empty stomach (1 hour before or 2 hours after a meal)
• take with a full (8 oz.) glass of water
• find right dose on chart below. If possible, use weight to dose; otherwise, use age.

adults and children 12 years and over | 2 tablets after the first loose stool; 1 tablet after each subsequent loose stool; but no more than 4 tablets in 24 hours
children 9-11 years (60-95 lbs) | 1 tablet after the first loose stool; 1/2 tablet after each subsequent loose stool; but no more than 3 tablets in 24 hours
children 6-8 years (48-59 lbs) | 1 tablet after the first loose stool; 1/2 tablet after each subsequent loose stool; but no more than 2 tablets in 24 hours
children 2-5 years (34 to 47 lbs) | ask a doctor
children under 2 years (up to 33 lbs) | do not use

OTHER INFORMATION

• each tablet contains: calcium 640 mg, very low sodium and potassium 5.838 mg
• store between 20 to 25°C (68 to 77°F). Protect from light.
• do not use if carton is open or if blister unit is open or torn

INACTIVE INGREDIENTS

acesulfame potassium, croscarmellose sodium, dibasic calcium phosphate, microcrystalline cellulose, stearic acid and vanilla flavor

PACKAGE LABEL

Loperamide Hydrochloride and Simethicone Tablets 2 mg/125 mg